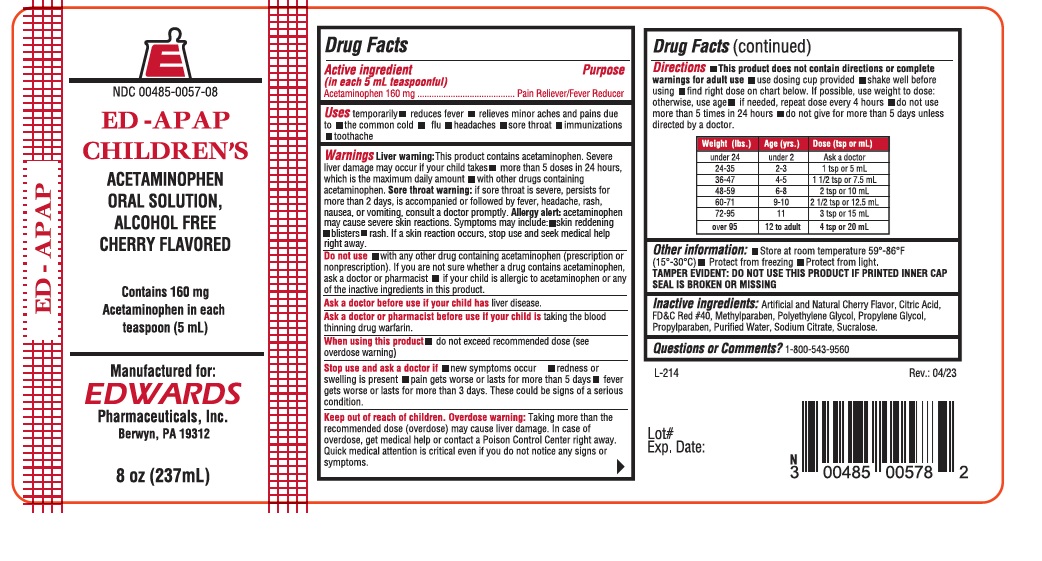 DRUG LABEL: ED APAP
NDC: 0485-0057 | Form: LIQUID
Manufacturer: EDWARDS PHARMACEUTICALS, INC.
Category: otc | Type: HUMAN OTC DRUG LABEL
Date: 20251231

ACTIVE INGREDIENTS: ACETAMINOPHEN 160 mg/5 mL
INACTIVE INGREDIENTS: PROPYLPARABEN; SUCRALOSE; FD&C RED NO. 40; METHYLPARABEN; POLYETHYLENE GLYCOL, UNSPECIFIED; SODIUM CITRATE; CITRIC ACID MONOHYDRATE; WATER; PROPYLENE GLYCOL

Ed-EdAPAPChild 0057

Drug Facts

Active ingredient (in each 5mL = 1 teaspoon)

Acetaminophen 160 mg

Purpose

Pain Reliever / Fever Reducer

Uses

temporarily:

- reduces fever
- relieves minor aches and pains due to:
  - the common cold
  - flu
  - headaches
  - sore throat
  - immunizations
  - toothache

Warnings

Liver warning

This product contains acetaminophen. Severe liver damage may occur if your child takes

- more than 5 doses in 24 hours, which is the maximum daily amount
- with other drugs containing acetaminophen.

Sore throat warning

if sore throat is severe, persists for more than 2 days, is accompanied or followed by fever, headache, rash, nausea, or vomiting, consult a doctor promptly.

Do not use

- with any other drug containing acetaminophen (prescription or non-prescription). If you are not sure whether a drug contains acetaminophen, ask a doctor or pharmacist.
- if your child is allergic to acetaminophen or any of the inactive ingredients in this product.

Ask a doctor before use if your child hasliver disease.

Ask a doctor or pharmacist before use if your child istaking the blood thinning drug warfarin.

When using this product

- do not exceed recommended dose (see overdose warning)

Stop use and ask a doctor if

- new symptoms occur
- redness or swelling is present
- pain gets worse or lasts for more than 5 days
- fever gets worse or lasts for more than 3 days. These could be signs of a serious condition.

Keep out of reach of children.

Overdose warning

Taking more than the recommended dose (overdose) may cause liver damage. In case of overdose, get medical help or contact a Poison Control Center right away. Quick medical attention is critical even if you do not notice any signs or symptoms.

Directions

- This product does not contain directions or complete warnings for adult use
- shake well before using
- find right dose on chart below. If possible, use weight to dose: otherwise, use age.
- if needed,repeat dose every 4 hours
- do not use more than 5 times in 24 hours
- do not give more than 5 days unless directed by a doctor.

Weight (lbs.) | Age (yrs.) | Dose (tsp or mL)
under 24 | under 2 | Ask a doctor
24-35 | 2-3 | 1 tsp or 5 mL
36-47 | 4-5 | 1 1/2 tsp or 7.5 mL
48-59 | 6-8 | 2 tsp or 10 mL
60-71 | 9-10 | 2 1/2 tsp or 12.5 mL
72-95 | 11 | 3 tsp or 15 mL

Other information

- Store at room temperature 15°-30° C (59°-86° F)
- Protect from freezing
- Protect from Light.
- Each teaspoon (5mL) contains:sodium 7 mg

TAMPER EVIDENT: DO NOT USE THIS PRODUCT IF PRINTED INNER CAP SEAL IS BROKEN OR MISSING.

Inactive ingredients

Artificial and Natural cherry flavor, citric acid, FD&C Red #40, Methylparaben, polyethylene glycol, propylene glycol, propylparaben, purified water, sodium citrate, sucralose

QUESTIONS? COMMENTS?

Call 1-800-543-9560

PRINCIPAL DISPLAY PANEL - 236 ml Bottle Label

E

NDC 00485-0057-08

ED-APAP
CHILDREN'S

ACETAMINOPHEN
ORAL SOLUTION,
ALCOHOL FREE
CHERRY FLAVORED

Contains 160 mg
Acetaminophen in each
teaspoon (5mL)

8 fl oz (236 ml)

Manufactured for:

EDWARDS
PHARMACEUTICALS, INC.
111 Mulberry Street
RIPLEY, MS 38663